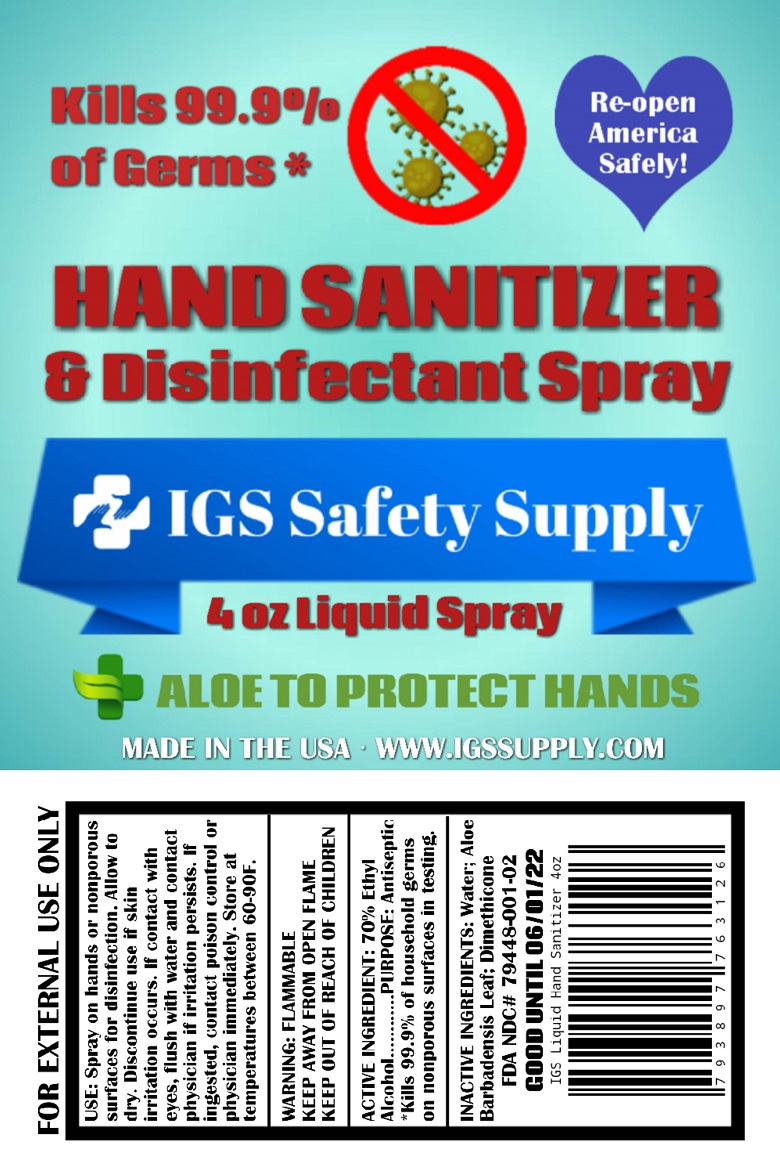 DRUG LABEL: IGS Safety Supply
NDC: 79448-001 | Form: LIQUID
Manufacturer: Innovative Global Solutions LLC dba IGS
Category: otc | Type: HUMAN OTC DRUG LABEL
Date: 20200720

ACTIVE INGREDIENTS: ALCOHOL 70 mL/100 mL
INACTIVE INGREDIENTS: PEG/PPG-18/18 DIMETHICONE; ALOE VERA LEAF; WATER

Active Ingredient

70% Ethyl alcohol.

Kills 99.9% of household germs on nonporous surfaces in testing.

Purpose

Antiseptic

Use

Spray on hands and nonporous surfaces for disinfection. Allow to dry.
Discontinue use if skin irritation occurs.
If contact with eyes, flush with water and contact physician if irritation persists.
If ingested, contact poison control or physician immediately. Store at temperatures between 60-90F.

Warnings

Flammable. Keep away from open flame.

Keep out of reach of children.

Inactive ingredients

Water, Aloe Barbadensis Leaf, Dimethicone